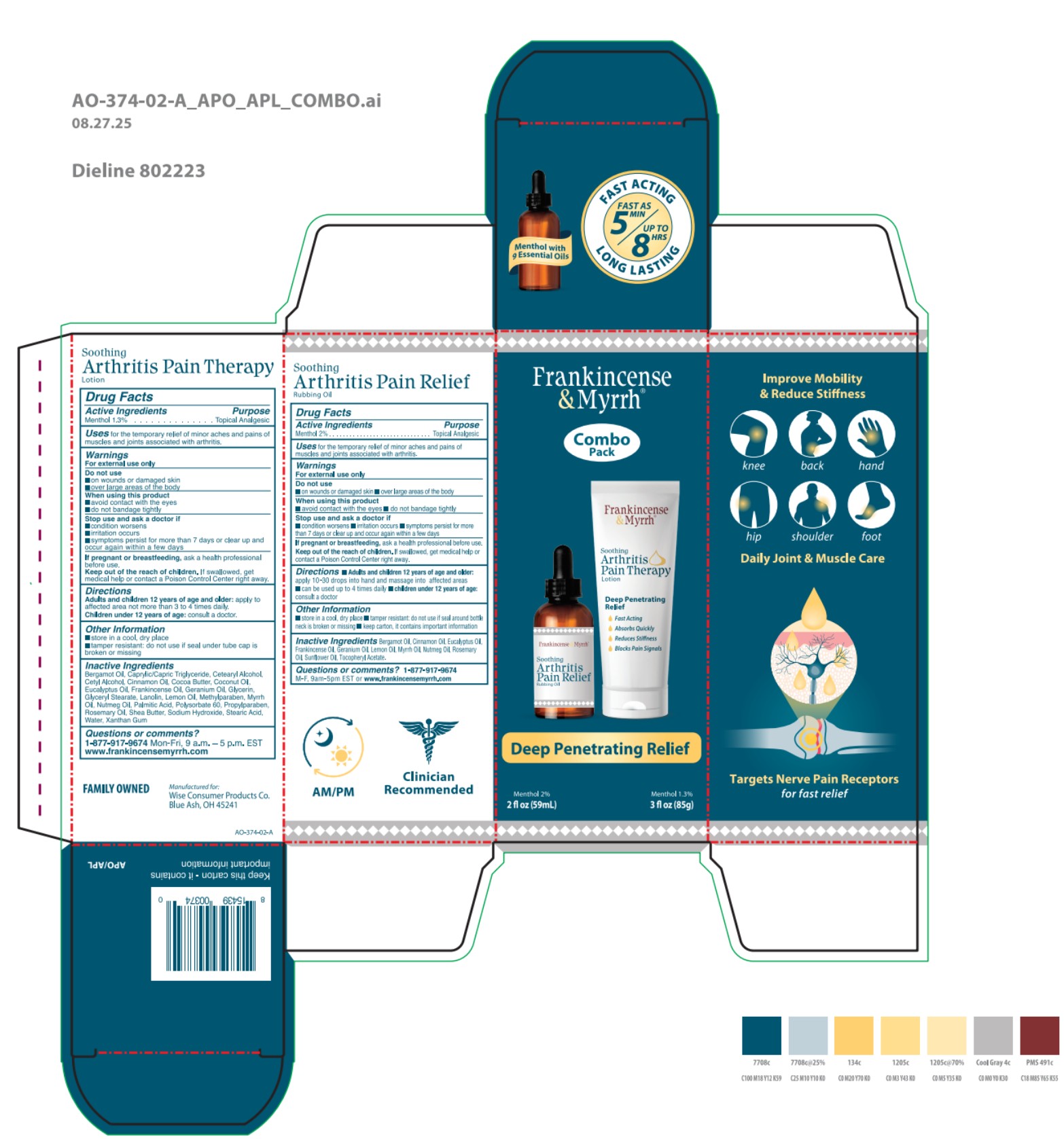 DRUG LABEL: Frankincense and Myrrh Arthritis Pain Combo Pack
NDC: 42346-374 | Form: KIT | Route: TOPICAL
Manufacturer: WISE CONSUMER PRODUCTS CO.
Category: otc | Type: HUMAN OTC DRUG LABEL
Date: 20251229

ACTIVE INGREDIENTS: MENTHOL 20 mg/1 mL; MENTHOL 1.3 g/100 g
INACTIVE INGREDIENTS: EUCALYPTUS OIL; FRANKINCENSE OIL; MYRRH OIL; CINNAMON LEAF OIL; NUTMEG OIL; GERANIUM OIL, ALGERIAN TYPE; ROSEMARY OIL; ALPHA-TOCOPHEROL ACETATE; BERGAMOT OIL; SUNFLOWER OIL; LEMON OIL; LEMON OIL, COLD PRESSED; GERANIUM OIL, ALGERIAN TYPE; COCOA BUTTER; CETOSTEARYL ALCOHOL; EUCALYPTUS OIL; GLYCERIN; PHENOXYETHANOL; CINNAMON LEAF OIL; LANOLIN; FRANKINCENSE OIL; NUTMEG OIL; COCONUT OIL; POLYSORBATE 60; GLYCERYL MONOSTEARATE; WATER; SHEA BUTTER; CETYL ALCOHOL; ROSEMARY OIL; MEDIUM-CHAIN TRIGLYCERIDES; XANTHAN GUM; MYRRH OIL; STEARYL ALCOHOL; BERGAMOT OIL

Frankincense and Myrrh Arthritis Pain Combo Pack

42346-726-59

Active ingredient

Menthol 2%

Purpose

Menthol 2% . . . . . . . . . . . . . . . . . . . . . . . . Topical Analgesic

Uses

for temporary relief of minor aches and pains of muscles and joints.

Warnings

For external use only.

Do not use

 on wounds or damaged skin

 over large areas of the body

When using this product

 avoid contact with the eyes

 do not bandage tightly

Stop use and ask a doctor if

 condition worsens

 irritation occurs

 symptoms persist for more than 7 days or clear up and occur again within a few days

PREGNANCY OR BREAST FEEDING

If pregnant or breastfeeding, ask a health professional before use.

KEEP OUT OF REACH OF CHILDREN

Keep out of the reach of children. If swallowed, get medical help or contact a Poison Control Center right away.

Directions

 Adults and children 12 years of age and older: apply 10-30 drops into hand and massage into affected areas

 can be used up to 4 times daily

 children under 12 years of age: consult a doctor

Other information

 store in a cool, dry place

 tamper resistant: do not use if seal around bottle neck is broken or missing

 keep carton, it contains important information

Inactive ingredients

Helianthus Annuus (Sunflower) Seed Oil, Eucalyptus Globulus Leaf Oil, Rosmarinus Officinalis (Rosemary) Leaf Oil, Pelargonium Graveolens (Geranium) Leaf Oil, Cinnamomum Zeylanicum (Cinnamon) Leaf Oil, Citrus Limon (Lemon) Peel Oil, Myristica Fragrans (Nutmeg) Kernel Oil, Citrus Aurantium Bergamia (Bergamot) Fruit Oil, Boswellia Carterii (Frankincense) Oil, Commiphora Myrrha (Myrrh) Oil, Tocopheryl Acetate.

Questions or comments?

1-877-917-9674
M-F, 9am-5pm EST or www.frankincensemyrrh.com

42346-731-85

Active ingredient

Menthol 1.3%

Purpose

Menthol 1.3%............................Topical Analgesic

Uses

For the temporary relief of minor aches and pains of muscles and joints associted with arthritis.

Warnings

For external use only

Do not use

- on woulds or damaged skin
- over large areas of the body

When using this product

- avoid contact with the eyes
- do not bandage tightly

Stop use and ask a doctor if

- condition worsens
- irritation occurs
- symptoms persist for more than 7 days or clear up and occur again within a few days

PREGNANCY OR BREAST FEEDING

If pregnant or breastfeeding, ask a health professional before use.

KEEP OUT OF REACH OF CHILDREN

Keep out of the reach of children. If swallowed, get medical help or contact a Poison Control Center right away.

Directions

Adults and children 12 years of age and older: apply to affected area no more than 3 to 4 times daily.

Children under 12 years of age: consult a doctor.

Other information

- store in a cool, dry place
- tamper resistant: do not use if seal under tube cap is broken or missing

Inactive ingredients

Water, Caprylic/Capric Triglyceride, Cocos Nucifera (Coconut) Oil, Butyrospermum Parkii (Shea) Butter, Lanolin, Cetearyl Alcohol, Glycerin, Theobroma Cacao (Cocoa) Seed Butter, Cetyl Alcohol, Stearyl Alcohol, Glyceryl Stearyl, Rosmarinus Officinalis (Rosemary) Lear Oil, Polysorbate 60, Eucalyptus Globulus Leaf Oil, Pelargonium Graveolens (Geranium) Oil, Phenoxyethanol, Xanthan Gum, Cinnamomum Zeylanicum (Cinnamon) Leaf Oil, Citrus Aurantium Bergamia (Bergamot) Fruit Oil, Myristica Fragrans (Nutmeg) Kernel Oil, Boswellia Carterii (Frankincense) Oil, Commuphora Myrrha (Myrrh) Oil, Citrus Medica Limonum (Lemon) Peel Oil

Questions or comments?

1-877-917-9674 Mon-Fri, 9 a.m. - 5 p.m. EST

www.frankincensemyrrh.com

PACKAGE LABEL

Frankincense & Myrrh

Combo Pack

Deep Penetrating Relief

Menthol 2%

2 fl oz (59 mL)

Menthol 1.3%

3 fl oz (85g)